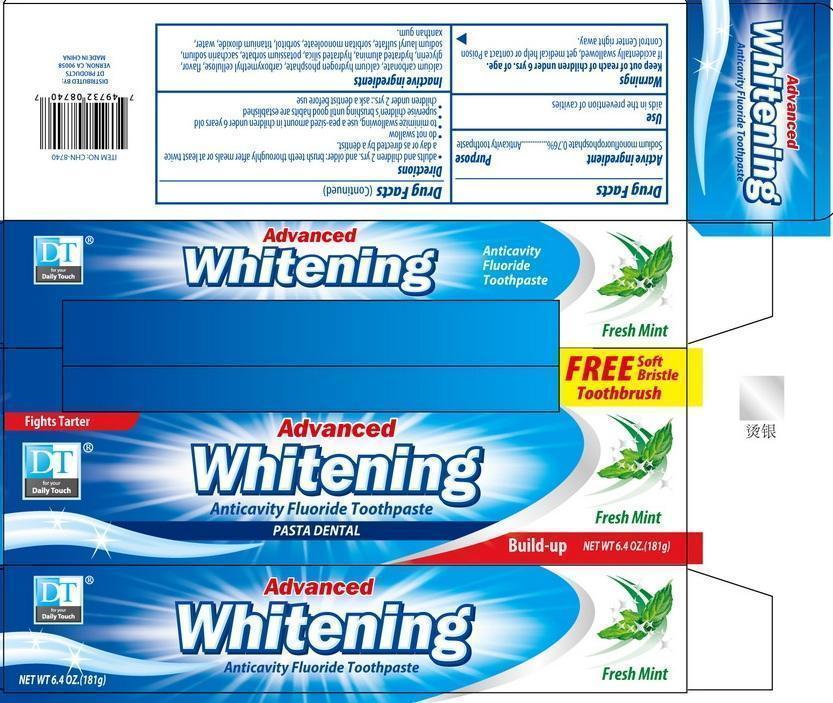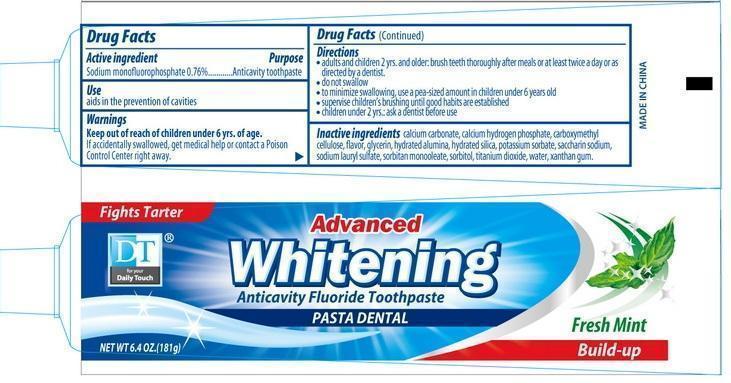 DRUG LABEL: DT Whitening Anticavity Fluoride
NDC: 50523-740 | Form: PASTE, DENTIFRICE
Manufacturer: Volume Distributors, Inc.
Category: otc | Type: HUMAN OTC DRUG LABEL
Date: 20180216

ACTIVE INGREDIENTS: SODIUM MONOFLUOROPHOSPHATE 0.1 g/100 g
INACTIVE INGREDIENTS: CALCIUM CARBONATE; ANHYDROUS DIBASIC CALCIUM PHOSPHATE; POWDERED CELLULOSE; GLYCERIN; ALUMINUM OXIDE; HYDRATED SILICA; POTASSIUM SORBATE; SACCHARIN SODIUM; SODIUM LAURYL SULFATE; SORBITAN MONOOLEATE; SORBITOL; TITANIUM DIOXIDE; WATER; XANTHAN GUM

DT WHITENING ANTICAVITY FLUORIDE TOOTHPASTE

Active Ingredient

Sodium Monofluorophosphate 0.76%

Purpose

Anticavity toothpaste

Uses

Aids in the prevention of cavities

Warnings

If accidentally swallowed, get medical help or contact a Poison Control Center right away.

Keep out of reach of children under 6 yrs of age.

Directions

adults and children 2 years. and older: brush teeth thoroughly after meals or at least twice a day or as directed by a dentist.

do not swallow

to minimize swallowing, use a pea-sized amount in children under 6 years old

supervise children's brushing until good habits are established

children under 2y ears: ask a dentist before use.

Directions

Inactive ingredients-

calcium carbonate, calcium hydrogen phosphate, carboxymethyl cellulose, flavor, glycerin, hydrated alumina, hydrated silica, potassium sorbate, saccharin sodium, sodium lauryl sulfate, sorbitan monooleate, sorbitol, titanium dioxide, water, xanthan gum.

Distributed by:

DT Products Vernon, CA 90058
Made in China

PACKAGE LABEL

DT Advanced Whitening Anticavity Fluoride Toothpaste

Net Wt 6.4oz (181g)

Fresh Mint